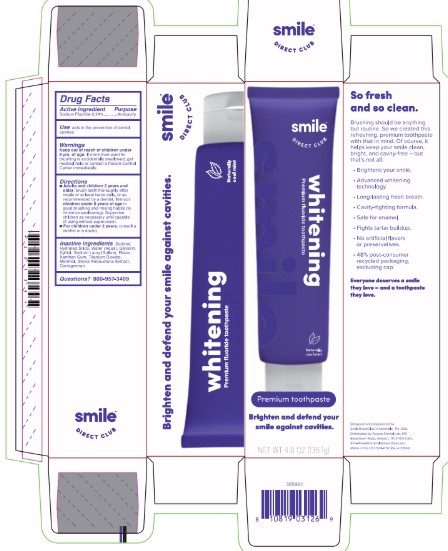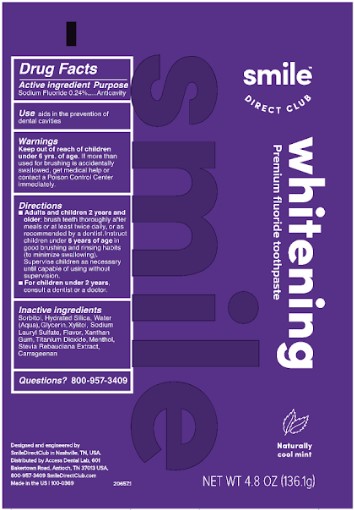 DRUG LABEL: Smile Direct Club
NDC: 73333-125 | Form: PASTE, DENTIFRICE
Manufacturer: Nutrix International, LLC
Category: otc | Type: HUMAN OTC DRUG LABEL
Date: 20200116

ACTIVE INGREDIENTS: SODIUM FLUORIDE 2.4 mg/1 g
INACTIVE INGREDIENTS: GLYCERIN; HYDRATED SILICA; WATER; XYLITOL; SODIUM LAURYL SULFATE; MINT; TITANIUM DIOXIDE; XANTHAN GUM; STEVIA REBAUDIUNA LEAF; CARRAGEENAN; SORBITOL; MENTHOL

Active Ingredient

Sodium Fluoride 0.24%

Purpose

Anticavity.

Indications and Usage Section

Aids in the prevention of dental cavities.

Warnings

If more than used for brushing is accidentally swallowed, get medical help or contact a Poison Control Center immedieately.

Keep out of reach of children under 6 year of age.

Directions

- Adults and children 2 years of age and older. Brush teeth thoroughly, preferably after each meal or at least twice a day, or as directed by a dentist or doctor.

- Instruct children under 6 years of age in good brushing and rinsing habits (to minimize swallowing).

- Supervise children as necessary until capable of using without supervision.

- Children under 2 years of age. Consult a dentist or doctor.

Inactive Ingredients

Sorbitol, Hydrated Silica, Water (Agua), Glycerin, Xylitol, Sodium Lauryl Sulfate, Flavor, Xanthan Gum,Titanium Dioxide, Menthol, Stevia Rebaudiana Extract, Carrageenan.

Questions?

800-957-3409